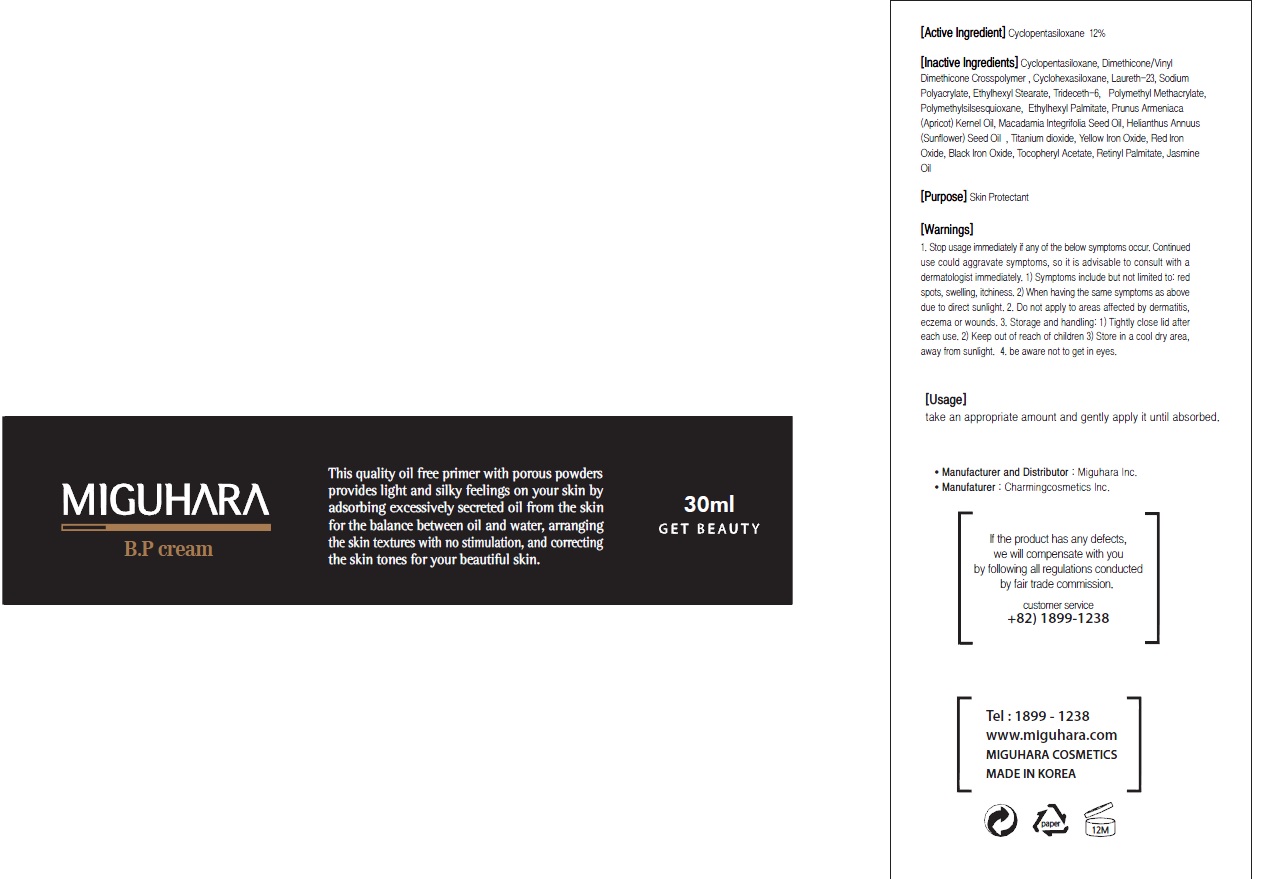 DRUG LABEL: BP
NDC: 70380-140 | Form: CREAM
Manufacturer: MIGUHARA
Category: otc | Type: HUMAN OTC DRUG LABEL
Date: 20160219

ACTIVE INGREDIENTS: CYCLOMETHICONE 5 3.6 g/30 mL
INACTIVE INGREDIENTS: Laureth-23; ETHYLHEXYL STEARATE

ACTIVE INGREDIENT

Active Ingredient: Cyclopentasiloxane 12%

INACTIVE INGREDIENT

Inactive Ingredients: Dimethicone/Vinyl Dimethicone Crosspolymer , Cyclohexasiloxane, Laureth-23, Sodium Polyacrylate, Ethylhexyl Stearate, Trideceth-6, Polymethyl Methacrylate, Polymethylsilsesquioxane, Ethylhexyl Palmitate, Prunus Armeniaca (Apricot) Kernel Oil, Macadamia Integrifolia Seed Oil, Helianthus Annuus (Sunflower) Seed Oil , Titanium dioxide, Yellow Iron Oxide, Red Iron Oxide, Black Iron Oxide, Tocopheryl Acetate, Retinyl Palmitate, Jasmine Oil

PURPOSE

Purpose: Skin Protectant

WARNINGS

1. Stop usage immediately if any of the below symptoms occur. Continued use could aggravate symptoms, so it is advisable to consult with a dermatologist immediately. 1) Symptoms include but not limited to: red spots, swelling, itchiness. 2) When having the same symptoms as above due to direct sunlight. 2. Do not apply to areas affected by dermatitis, eczema or wounds. 3. Storage and handling: 1) Tightly close lid after each use. 2 Keep out of reach of children 3) Store in a cool dry area, away from sunlight 4. be aware not to get in eyes.

KEEP OUT OF REACH OF CHILDREN

Usage

Usage: Take an appropriate amount and gently apply it until absorbed.

Usage

Usage: Take an appropriate amount and gently apply it until absorbed.